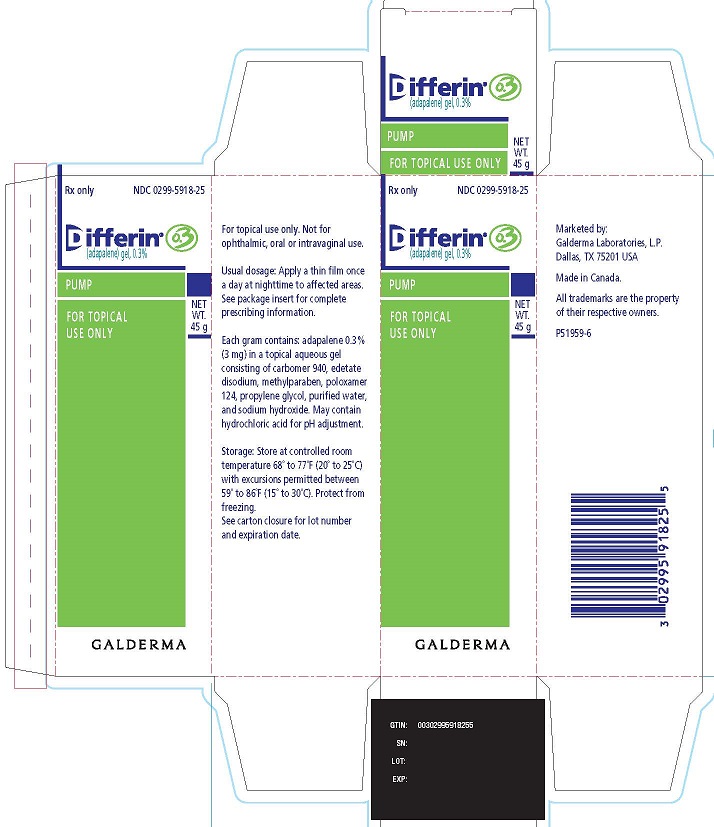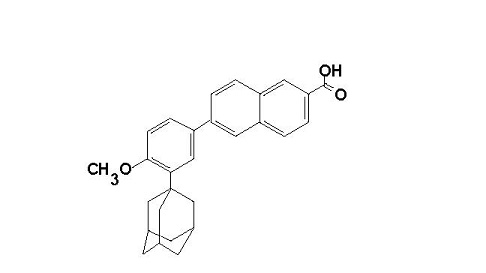 DRUG LABEL: DIFFERIN
NDC: 0299-5918 | Form: GEL
Manufacturer: Galderma Laboratories, L.P.
Category: prescription | Type: HUMAN PRESCRIPTION DRUG LABEL
Date: 20231227

ACTIVE INGREDIENTS: Adapalene 3 mg/1 g
INACTIVE INGREDIENTS: Carbomer Homopolymer Type C; Edetate Disodium; Methylparaben; Propylene Glycol; Water; Sodium Hydroxide; Hydrochloric Acid; Poloxamer 124

HIGHLIGHTS OF PRESCRIBING INFORMATION

These highlights do not include all the information needed to use DIFFERIN Gel safely and effectively. See full prescribing information for DIFFERIN Gel.
DIFFERIN® (adapalene) gel, for topical use
Initial U.S. Approval: 1996

1 INDICATIONS AND USAGE

DIFFERIN Gel, 0.3%, is a retinoid, indicated for the topical treatment of acne vulgaris in patients 12 years of age and older. (1)

2 DOSAGE AND ADMINISTRATION

- Wash affected areas gently with a non-medicated soap. (2)
- Apply a thin film of DIFFERIN Gel, to the entire face and other affected areas of the skin once daily in the evening. (2) For topical use only. Not for ophthalmic, oral or intravaginal use. (2)

3 DOSAGE FORMS AND STRENGTHS

Gel, 0.3% (3)

4 CONTRAINDICATIONS

Contraindicated in patients who have known hypersensitivity to adapalene or any excipient of DIFFERIN Gel. (4)

5 WARNINGS AND PRECAUTIONS

- Allergic/ Hypersensitivity Reactions: Allergy/hypersensitivity reactions include anaphylaxis angioedema, face edema, eyelid edema, lip swelling, and pruritis. Discontinue DIFFERIN Gel in the event of an allergic/hypersensitivity reaction.(5.1)
- Ultraviolet Light and Environmental Exposure: Avoid exposure to sunlight and sunlamps. Wear sunscreen when sun exposure cannot be avoided (5.2).
- Local Cutaneous Reactions: Erythema, scaling, dryness, and stinging/burning were reported with use of DIFFERIN Gel. Concomitant use of other potentially irritating topical products (medicated or abrasive soaps and cleansers, soaps and cosmetics that have a strong drying effect and products with high concentrations of alcohol, astringents, spices, or lime) should be approached with caution. (5.3).

6 ADVERSE REACTIONS

The most frequently reported (≥ 1%) adverse reactions were erythema, scaling, dryness, and/or burning/stinging. (6.1)
To report SUSPECTED ADVERSE REACTIONS, contact Galderma Laboratories, L.P. at 1-866-735-4137 or FDA at 1-800-FDA-1088 or www.fda.gov/medwatch.

FULL PRESCRIBING INFORMATION

1 INDICATIONS AND USAGE

DIFFERIN Gel is indicated for the topical treatment of acne vulgaris in patients 12 years of age and older.

2 DOSAGE AND ADMINISTRATION

Wash affected areas gently with a non-medicated soap. Apply a thin film of DIFFERIN Gel to the entire face and any other affected areas of the skin once daily in the evening. Avoid application to the areas of skin around eyes, lips, and mucous membranes. A mild transitory sensation of warmth or slight stinging may occur shortly after the application of DIFFERIN Gel.
Instruct patients to minimize sun exposure and to use moisturizers for relief of dry skin or irritation.

If therapeutic results are not noticed after 12 weeks of treatment, therapy should be re-evaluated.

For topical use only. Not for ophthalmic, oral or intravaginal use.

3 DOSAGE FORMS AND STRENGTHS

Each gram of DIFFERIN Gel, 0.3% contains 3 mg adapalene in an off-white aqueous gel.

4 CONTRAINDICATIONS

DIFFERIN Gel is contraindicated in patients who have known hypersensitivity to adapalene or any excipient of DIFFERIN Gel [see WARNINGS AND PRECAUTIONS (5.1)].

5 WARNINGS AND PRECAUTIONS

5.1 Allergic/ Hypersensitivity Reactions

Adverse reactions including anaphylaxis angioedema, face edema, eyelid edema, lip swelling, and pruritus that sometimes required medical treatment have been reported during postmarketing use of adapalene. Advise a patient to stop using DIFFERIN Gel and seek medical attention if experiencing allergic or anaphylactoid/anaphylactic reactions during treatment.

5.2 Ultraviolet Light and Environmental Exposure

Exposure to sunlight, including sunlamps, should be minimized during use of DIFFERIN Gel. Patients who normally experience high levels of sun exposure, and those with inherent sensitivity to sun, should be warned to exercise caution. Use of sunscreen products and protective clothing over treated areas is recommended when exposure cannot be avoided. Weather extremes, such as wind or cold, also may be irritating to patients under treatment with DIFFERIN Gel.

5.3 Local Cutaneous Reactions

Cutaneous signs and symptoms such as erythema, scaling, dryness, and stinging/burning were reported with use of DIFFERIN Gel. These were most likely to occur during the first four weeks of treatment, were mostly mild to moderate in intensity, and usually lessened with continued use of the medication. Depending upon the severity of these side effects, patients should be instructed to either use a moisturizer, reduce the frequency of application of DIFFERIN Gel or discontinue use.

Avoid application to cuts, abrasions, eczematous or sunburned skin. As with other retinoids, use of “waxing” as a depilatory method should be avoided on skin treated with adapalene.

As DIFFERIN Gel has the potential to induce local irritation in some patients, concomitant use of other potentially irritating topical products (medicated or abrasive soaps and cleansers, soaps and cosmetics that have a strong drying effect and products with high concentrations of alcohol, astringents, spices, or lime) should be approached with caution.

6 ADVERSE REACTIONS

6.1 Clinical Trials Experience

Because clinical trials are conducted under widely varying conditions, adverse reactions rates observed in the clinical trials of a drug cannot be directly compared to rates in the clinical trials of another drug and may not reflect the rates observed in practice.

In the multi-center, controlled clinical trial, signs and symptoms of local cutaneous irritation were monitored in 258 acne subjects who used DIFFERIN Gel once daily for 12 weeks. Of the subjects who experienced cutaneous irritation (erythema, scaling, dryness, and/or burning/stinging), the majority of cases were mild to moderate in severity, occurred early in treatment and decreased thereafter. The incidence of local cutaneous irritation with DIFFERIN Gel from the controlled clinical trial is provided in the following table:

Table 1: Physician assessed local cutaneous irritation with DIFFERIN Gel
Incidence of Local Cutaneous Irritation with DIFFERIN Gel
(N = 253*)
Maximum Severity Scores Higher Than Baseline
 | Mild | Moderate | Severe
Erythema | 66 (26.1%) | 33 (13.0%) | 1 (0.4%)
Scaling | 110 (43.5%) | 47 (18.6%) | 3 (1.2%)
Dryness | 113 (44.7%) | 43 (17.0%) | 2 (0.8%)
Burning/Stinging | 72 (28.5%) | 36 (14.2%) | 9 (3.6%)

* Total number of subjects with local cutaneous data for at least one post-Baseline evaluation

Table 2: Patient reported local cutaneous reactions with DIFFERIN Gel
 | DIFFERIN (adapalene) Gel | Vehicle Gel
 | N = 258 | N = 134
Related* Adverse Reactions Dry Skin Skin Discomfort Desquamation | 57 (22.1%) 36 (14%) 15 (5.8%) 4 (1.6%) | 6 (4.5%) 2 (1.5%) 0 (0%) 0 (0%)

* Selected adverse reactions defined by investigator as Possibly, Probably or Definitely Related

The following adverse reactions occurred in less than 1% of subjects: acne flare, contact dermatitis, eyelid edema, conjunctivitis, erythema, pruritus, skin discoloration, rash, and eczema.

In a one-year, open-label safety trial of 551 subjects with acne who received DIFFERIN Gel, the pattern of adverse reactions was similar to the 12-week controlled study.

6.2 Post-Marketing Experience

The following adverse reactions have been identified during post approval use of adapalene:
Immune system disorders: angioedema, face edema, lip swelling
Skin disorders: application site pain
Because these reactions are reported voluntarily from a population of uncertain size, it is not always possible to reliably estimate the frequency or establish a causal relationship to drug exposure.

8 USE IN SPECIFIC POPULATIONS

8.1 Pregnancy

Risk Summary
Available data from clinical trials with DIFFERIN Gel use in pregnant women are insufficient to establish a drug-associated risk of major birth defects, miscarriage or other adverse maternal or fetal outcomes. In animal reproduction studies, oral administration of adapalene to pregnant rats and rabbits during organogenesis at dose exposures 40 and 81 times, respectively, the human exposure at the maximum recommended human dose (MRHD) of 2 g resulted in fetal skeletal and visceral malformations (see Data).
The background risk of major birth defects and miscarriage for the indicated population is unknown. All pregnancies have a background risk of birth defects, loss, or other adverse outcomes. In the U.S. general population the estimated background risk of major birth defects and miscarriage in clinically recognized pregnancies are 2 to 4% and 15 to 20%, respectively.

Data

Animal Data
No malformations were observed in rats treated with oral adapalene doses of 0.15 to 5.0 mg/kg/day, up to 8 times the MRHD based on a mg/m² comparison. However, malformations were observed in rats and rabbits when treated with oral doses of ≥ 25 mg/kg/day adapalene (40 and 81 times the MRHD, respectively, based on a mg/m² comparison). Findings included cleft palate, microphthalmia, encephalocele, and skeletal abnormalities in rats and umbilical hernia, exophthalmos, and kidney and skeletal abnormalities in rabbits.

Dermal adapalene embryofetal development studies in rats and rabbits at doses up to 6.0 mg/kg/day (9.7 and 19.5 times the MRHD, respectively, based on a mg/m^2 comparison) exhibited no fetotoxicity and only minimal increases in skeletal variations (supernumerary ribs in both species and delayed ossification in rabbits).

8.2 Lactation

Risk Summary
There are no data on the presence of topical adapalene gel or its metabolite in human milk, the effects on the breastfed infant, or the effects on milk production. In animal studies, adapalene is present in rat milk with oral administration of the drug. When a drug is present in animal milk, it is likely that the drug will be present in human milk. It is possible that topical administration of large amounts of adapalene could result in sufficient systemic absorption to produce detectable quantities in human milk (see Clinical Considerations). The developmental and health benefits of breastfeeding should be considered along with the mother's clinical need for DIFFERIN Gel and any potential adverse effects on the breastfed child from DIFFERIN Gel, or from the underlying maternal condition.
Clinical Considerations
To minimize potential exposure to the breastfed infant via breastmilk, use DIFFERIN Gel on the smallest area of skin and for the shortest duration possible while breastfeeding. Avoid application of DIFFERIN Gel to areas with increased risk for potential ingestion by or ocular exposure to the breastfeeding child.

8.4 Pediatric Use

Safety and effectiveness have not been established in pediatric patients below the age of 12.

8.5 Geriatric Use

Clinical studies of DIFFERIN Gel did not include subjects 65 years of age and older to determine whether they respond differently than younger subjects. Safety and effectiveness in geriatric patients age 65 and above have not been established.

10 OVERDOSAGE

Chronic ingestion of the drug may lead to the same side effects as those associated with excessive oral intake of vitamin A.

11 DESCRIPTION

DIFFERIN (adapalene) Gel contains adapalene 0.3% (3 mg/g) in a topical aqueous gel for use in the treatment of acne vulgaris, consisting of carbomer 940, edetate disodium, methylparaben, poloxamer 124, propylene glycol, purified water, and sodium hydroxide. May contain hydrochloric acid for pH adjustment.

The chemical name of adapalene is 6-[3-(1-adamantyl)-4-methoxyphenyl]-2-naphthoic acid. It is a white to off-white powder, which is soluble in tetrahydrofuran, very slightly soluble in ethanol, and practically insoluble in water. The molecular formula is C28H28O3 and molecular weight is 412.53. Adapalene is represented by the following structural formula.

12 CLINICAL PHARMACOLOGY

12.1 Mechanism of Action

Adapalene binds to specific retinoic acid nuclear receptors but does not bind to cytosolic receptor protein. Biochemical and pharmacological profile studies have demonstrated that adapalene is a modulator of cellular differentiation, keratinization, and inflammatory processes. However, the significance of these findings with regard to the mechanism of action of adapalene for the treatment of acne is unknown.

12.2 Pharmacodynamics

Clinical pharmacodynamic studies have not been conducted for DIFFERIN Gel.

12.3 Pharmacokinetics

Systemic exposure of adapalene following topical application of DIFFERIN Gel was evaluated in a clinical trial. Sixteen acne subjects were treated once daily for 10 days with 2 grams of DIFFERIN Gel applied to the face, chest and back, corresponding to approximately 2 mg/cm^2. Fifteen subjects had quantifiable (LOQ = 0.1 ng/mL) adapalene levels resulting in a mean Cmax of 0.553 ± 0.466 ng/mL on Day 10 of treatment. The mean AUC0-24hr was 8.37 ± 8.46 ng.h/mL as determined in 15 of the 16 subjects on Day 10. The terminal apparent half-life, determined in 15 of 16 subjects, ranged from 7 to 51 hours, with a mean of 17.2 ± 10.2 hours. Adapalene was rapidly cleared from plasma and was not detected 72 hours after the last application for all but one subject. Exposure of potential circulating metabolites of adapalene was not measured. Excretion of adapalene appears to be primarily by the biliary route.

In another clinical trial in subjects with moderate to moderately severe acne, DIFFERIN (adapalene) Gel, 0.3% or Adapalene Gel, 0.1% was applied to the face and optionally to the trunk, once daily for 12 weeks. Seventy-eight (78) subjects had plasma adapalene levels evaluated at Weeks 2, 8, and 12. Of the 209 plasma samples analyzed, adapalene concentrations were below the limit of detection (LOD = 0.15 ng/mL) of the method in all samples but three. For the three samples, traces of adapalene below the limit of quantification (LOQ = 0.25 ng/mL) of the method were found. One of these samples was taken at Week 12 from a male subject treated with DIFFERIN Gel, 0.3% who treated the face and the trunk for eight weeks (thereafter, only the face was treated). The second and third samples were from the Week 2 and 12 visits of a female subject treated with Adapalene Gel, 0.1% who treated only the face for 12 weeks. In this study, the average daily usage of product was 1 g/day.

13 NONCLINICAL TOXICOLOGY

13.1 Carcinogenesis, Mutagenesis, Impairment of Fertility

No carcinogenicity, genotoxicity, or impairment of fertility studies were conducted with DIFFERIN Gel.

Carcinogenicity studies with adapalene were conducted in mice at topical doses of 0.4, 1.3, and 4.0 mg/kg/day (1.2, 3.9, and 12 mg/m^2/day) and in rats at oral doses of 0.15, 0.5, and 1.5 mg/kg/day (0.9, 3.0, and 9.0 mg/m^2/day). The highest dose levels are 3.2 (mice) and 2.4 (rats) times the MRHD based on a mg/m^2 comparison. In the rat study, an increased incidence of benign and malignant pheochromocytomas reported in the adrenal medulla of male rats was observed.

Adapalene was not mutagenic or genotoxic in vitro (Ames test, Chinese hamster ovary cell assay, or mouse lymphoma TK assay) or in vivo (mouse micronucleus test).

In rat oral studies, 20 mg/kg/day adapalene (32 times the MRHD based on a mg/m^2 comparison) did not affect the reproductive performance and fertility of F0 males and females or the growth, development, or reproductive function of F1 offspring

14 CLINICAL STUDIES

The safety and efficacy of once daily use of DIFFERIN Gel for treatment of acne vulgaris were assessed in one 12 week, multi-center, controlled, clinical trial, conducted in a total of 653 subjects 12 to 52 years of age with acne vulgaris of mild to moderate severity. All female subjects of child-bearing potential enrolled in the trial were required to have a negative urine pregnancy test at the beginning of the trial and were required to practice a highly effective method of contraception during the trial. Female subjects who were pregnant, nursing or planning to become pregnant were excluded from the trial.

Subjects enrolled in the trial were Caucasian (72%), Hispanic (12%), African-American (10%), Asian (3%), and other (2%). An equal number of males (49.5%) and females (50.5%) enrolled. Success was defined as “Clear” or “Almost Clear” in the Investigator’s Global Assessment (IGA). The success rate, mean reduction, and percent reduction in acne lesion counts from Baseline after 12 weeks of treatment are presented in the following table:

Table 3: Clinical study primary efficacy results at Week 12
 | DIFFERIN (adapalene) Gel, 0.3% | Adapalene Gel, 0.1% | Vehicle Gel
 | N = 258 | N = 261 | N = 134
IGA Success Rate | 53 (21%) | 41 (16%) | 12 (9%)
Inflammatory Lesions Mean Baseline Count Mean Absolute (%) Reduction | 27.7 14.4 (51.6%) | 28.1 13.9 (49.7%) | 27.2 11.2 (40.7%)
Non-Inflammatory Lesions Mean Baseline Count Mean Absolute (%) Reduction | 39.4 16.3 (39.7%) | 41.0 15.2 (35.2%) | 40.0 10.3 (27.2%)
Total Lesions Mean Baseline Count Mean Absolute (%) Reduction | 67.1 30.6 (45.3%) | 69.1 29.0 (41.8%) | 67.2 21.4 (33.7%)

16 HOW SUPPLIED/ STORAGE AND HANDLING

DIFFERIN Gel, 0.3% is supplied in the following size.

45 g pump - NDC 0299-5918-25

Storage: Store at controlled room temperature 68° to 77°F (20° to 25°C) with excursions permitted between 59° to 86°F (15° to 30°C). Protect from freezing. Keep out of reach of children.

17 PATIENT COUNSELING INFORMATION

Advise the patient to read the FDA-approved patient labeling (Patient Information)

Information for Patients
Patients using DIFFERIN Gel should receive the following information and instructions:

1. Apply a thin film of DIFFERIN Gel to the entire face and any other affected areas of the skin once daily in the evening. Apply a thin film of DIFFERIN Gel to the entire face and any other affected areas of the skin once daily in the evening, after washing gently with a non-medicated soap.
2. Avoid contact with the eyes, lips, angles of the nose, and mucous membranes
3. Moisturizers may be used if necessary; however, products containing alpha hydroxy or glycolic acids should be avoided.
4. This medication should not be applied to cuts, abrasions, eczematous, or sunburned skin.
5. Wax depilation should not be performed on treated skin due to the potential for skin erosions.
6. Minimize exposure to sunlight including sunlamps. Recommend the use of sunscreen products and protective apparel (e.g., hat) when exposure cannot be avoided.
7. Contact the doctor if skin rash, pruritus, hives, chest pain, edema, and shortness of breath occurs, as these may be signs of allergy or hypersensitivity.
8. This product is for external use only.
9. Lactation: Use DIFFERIN Gel on the smallest area of skin and for the shortest duration possible while breastfeeding. Avoid application of DIFFERIN Gel to areas with increased risk for potential ingestion by or ocular exposure to the breastfeeding child. [See Use in Specific Populations, Lactation (8.2)]

Marketed by:
GALDERMA LABORATORIES, L.P., Dallas, TX 75201 USA
Manufactured by:G Production Inc., Baie d’Urfé, QC, H9X 3S4 Canada
Made in Canada.
GALDERMA is a registered trademark.
P52321-X

PATIENT INFORMATION

DIFFERIN® [Dif-er-in]
(adapalene)
Gel

Important: DIFFERIN Gel is for use on the skin only (topical). Do not use DIFFERIN Gel in or on your mouth, eyes, or vagina.

What is DIFFERIN Gel?
DIFFERIN Gel is a prescription medicine for skin use only (topical) used to treat acne vulgaris in people 12 years of age and older.
It is not known if DIFFERIN Gel is safe and effective in children under 12 years of age or in people 65 years of age and older.

Do not use DIFFERIN Gel if you are allergic to adapalene or any of the ingredients in DIFFERIN Gel. See the end of this Patient Information leaflet for a complete list of ingredients in DIFFERIN Gel.

Before using DIFFERIN Gel, tell your healthcare provider about all your medical conditions, including if you:

- have other skin problems, including cuts, abrasions, sunburn, or skin that is dry, itchy, or red
- are pregnant or plan to become pregnant. It is not known if DIFFERIN Gel, can harm your unborn baby.
- are breastfeeding or plan to breastfeed. It is not known if DIFFERIN Gel passes into your breast milk and if it can harm your baby. Talk to your healthcare provider about the best way to feed your baby if you use DIFFERIN Gel. If you use DIFFERIN Gel while breastfeeding, use DIFFERIN Gel on the smallest area of the skin and for the shortest time needed. Do not apply DIFFERIN Gel to areas that may increase the risk of getting DIFFERIN Gel in your child’s mouth or eyes.

Tell your healthcare provider about all the medicines you take, including prescription and over-the-counter medicines, vitamins, and herbal supplements.

How should I use DIFFERIN Gel?

- Use DIFFERIN Gel exactly as your healthcare provider tells you to use it.
- Apply DIFFERIN Gel 1 time a day in the evening.
- Tell your healthcare provider if you do not notice a difference in your acne after using DIFFERIN Gel for 12 weeks

Applying DIFFERIN Gel:

- Wash the area where DIFFERIN Gel will be applied with a mild soap that does not contain a medicine and pat dry.
- DIFFERIN Gel comes in a pump. If you have been prescribed the:
  - Pump: Depress the pump to dispense a small amount of DIFFERIN Gel and spread a thin layer over the entire face and any other affected area.
  - Do not apply DIFFERIN Gel on areas of the skin around your eyes, lips, nose, and mouth.
- Wash your hands after applying DIFFERIN Gel.

What should I avoid while using DIFFERIN Gel?

- Avoid spending time in sunlight, including sunlamps. DIFFERIN Gel can make your skin sensitive to the sun and the light from sunlamps. Use sunscreen and wear hat and clothes that cover the areas treated with DIFFERIN Gel if you have to be in sunlight.
- Cold weather and wind may irritate your skin treated with DIFFERIN Gel.
- Do not apply DIFFERIN Gel to cuts, abrasions, sunburned skin, or skin that is dry, itchy, or red.
- Avoid skin products that may dry or irritate your skin such as harsh soaps or cleansers, soaps and cosmetics that make your skin dry, and products that contain high levels of alcohol, astringents, spices, or limes.
- Avoid the use of “waxing” as a hair removal method on skin treated with DIFFERIN Gel.

What are the possible side effects of DIFFERIN Gel?
DIFFERIN Gel may cause serious side effects including:

- Allergic reactions. DIFFERIN Gel may cause serious allergic reactions that sometimes may require medical treatment. Stop using DIFFERIN Gel and tell your healthcare provider or get medical help right away if you have any of these symptoms of an allergic reaction:
  - skin rash, itching or hives
  - trouble breathing or chest pain
  - swelling of your face, eyes, lips, tongue, or throat
- Skin reactions at the treated site. DIFFERIN Gel may cause skin reactions including redness, scaling, dryness, stinging, and burning. These skin reactions are most likely to happen during the first 4 weeks of treatment, and usually lessen with continued use of DIFFERIN Gel. Your healthcare provider may tell you to use a moisturizer, decrease how often you use DIFFERIN Gel, or stop treatment with DIFFERIN Gel if you get any skin reactions. If you use a moisturizer, you should avoid moisturizers that contain alpha hydroxy or glycolic acid. Ask your healthcare provider or pharmacist if you are not sure.

The most common side effects of DIFFERIN Gel include dry skin, skin pain, itching, and skin peeling.
These are not all the possible side effects of DIFFERIN Gel.
Call your doctor for medical advice about side effects. You may report side effects to FDA at 1-800-FDA-1088.
You may also report side effects to GALDERMA LABORATORIES, L.P. at 1-866-735-4137.

How should I store DIFFERIN Gel?

- Store DIFFERIN Gel at room temperature between 68° F to 77° F (20° C to 25° C).
- Do not freeze DIFFERIN Gel.

Keep DIFFERIN Gel and all medicines out of the reach of children.
General information about the safe and effective use of DIFFERIN Gel.
Medicines are sometimes prescribed for purposes other than those listed in a Patient Information Leaflet. Do not use DIFFERIN Gel for a condition for which it was not prescribed. Do not give DIFFERIN Gel to other people, even if they have the same symptoms you have. It may harm them. You can also ask your pharmacist or healthcare provider for information about DIFFERIN Gel that is written for health professionals.

What are the ingredients in DIFFERIN Gel?
Active ingredient: adapalene
Inactive ingredients: carbomer 940, edetate disodium, methylparaben, poloxamer 124, propylene glycol, purified water and sodium hydroxide. May contain hydrochloric acid for pH adjustment.

Marketed by: GALDERMA LABORATORIES, L.P., Dallas, Texas 75201 USA
Made in Canada.
GALDERMA is a registered trademark.
P52321-X
Revised: 12/2023
This Patient Information has been approved by the U.S. Food and Drug Administration.

PACKAGE LABEL - 45 g PUMP

Rx only

NDC 0299-5918-25

Differin® 0.3
(adapalene) Gel, 0.3%

PUMP

FOR TOPICAL USE ONLY

NET WT. 45 g

Galderma

For topical use only. Not for ophthalmic, oral, or intravaginal use.

Usual dosage: apply a thin film once a day at nighttime to affected areas. See package insert for complete prescribing information.

Each gram contains: adapalene 0.3% (3 mg) in an aqueous gel consisting of carbomer 940, edetate disodium, methylparaben, poloxamer 124, propylene glycol, purified water, and sodium hydroxide. May contain hydrochloric acid for pH adjustment.

Storage: Store at controlled room temperature 68° to 77°F (20° to 25°C) with excursions permitted between 59° to 86°F (15° to 30°C). Protect from freezing.

See carton closure for lot number and expiration date.

Marketed by:
GALDERMA LABORATORIES, L.P.
Dallas, TX 75201 USA
Made in Canada
All trademarks are the property of their respective owners.
P51959-6